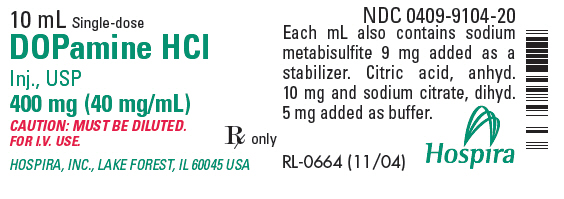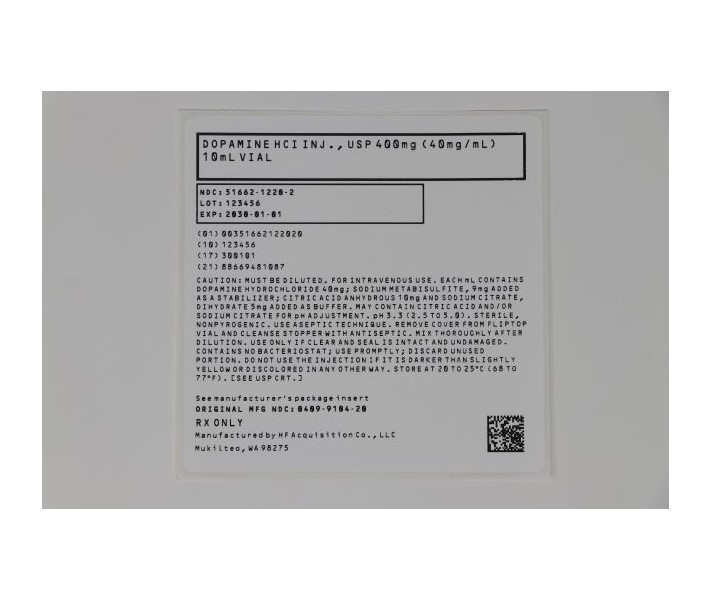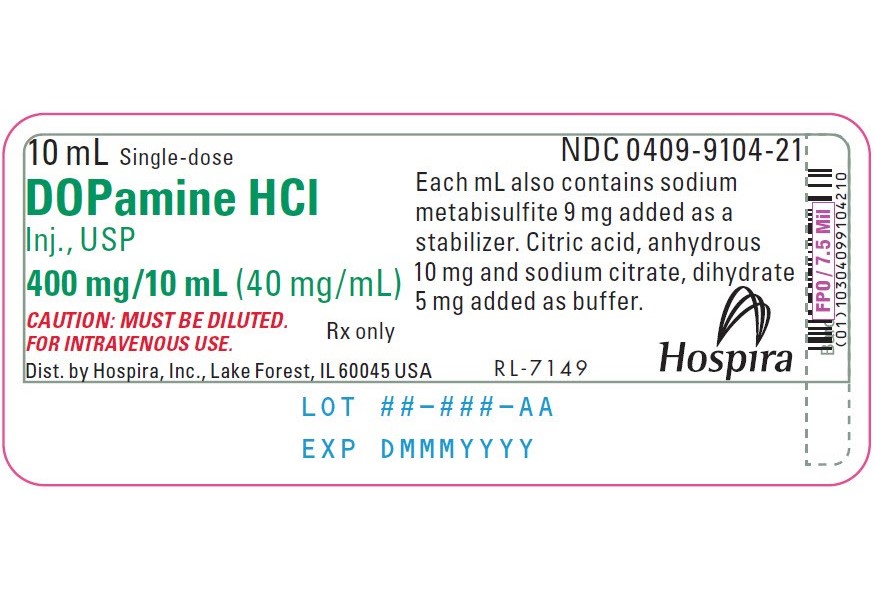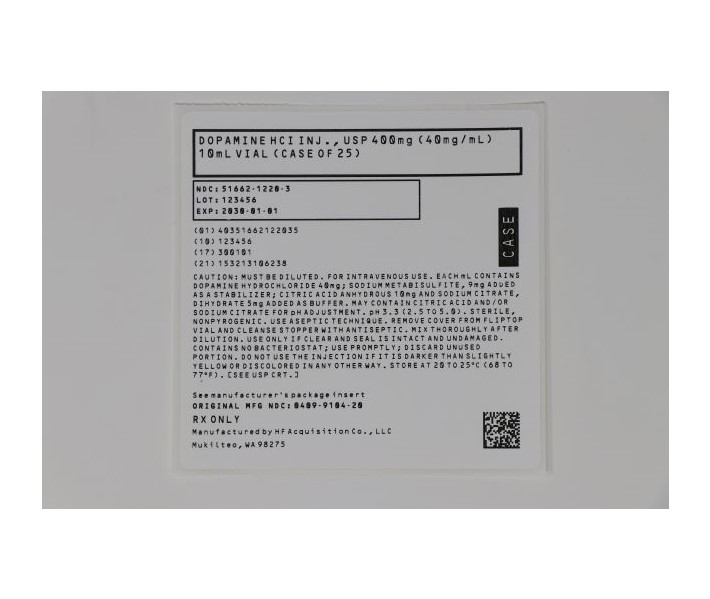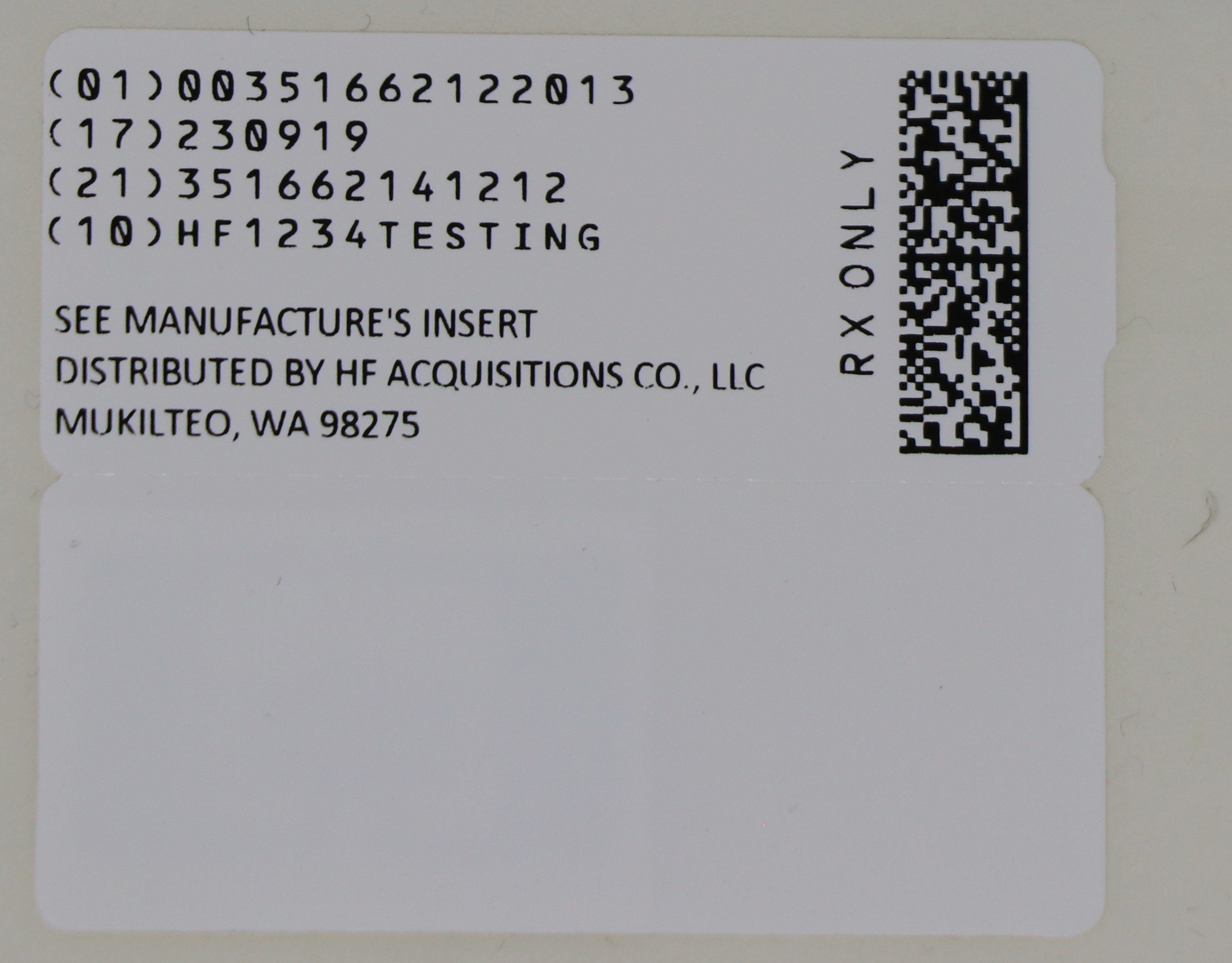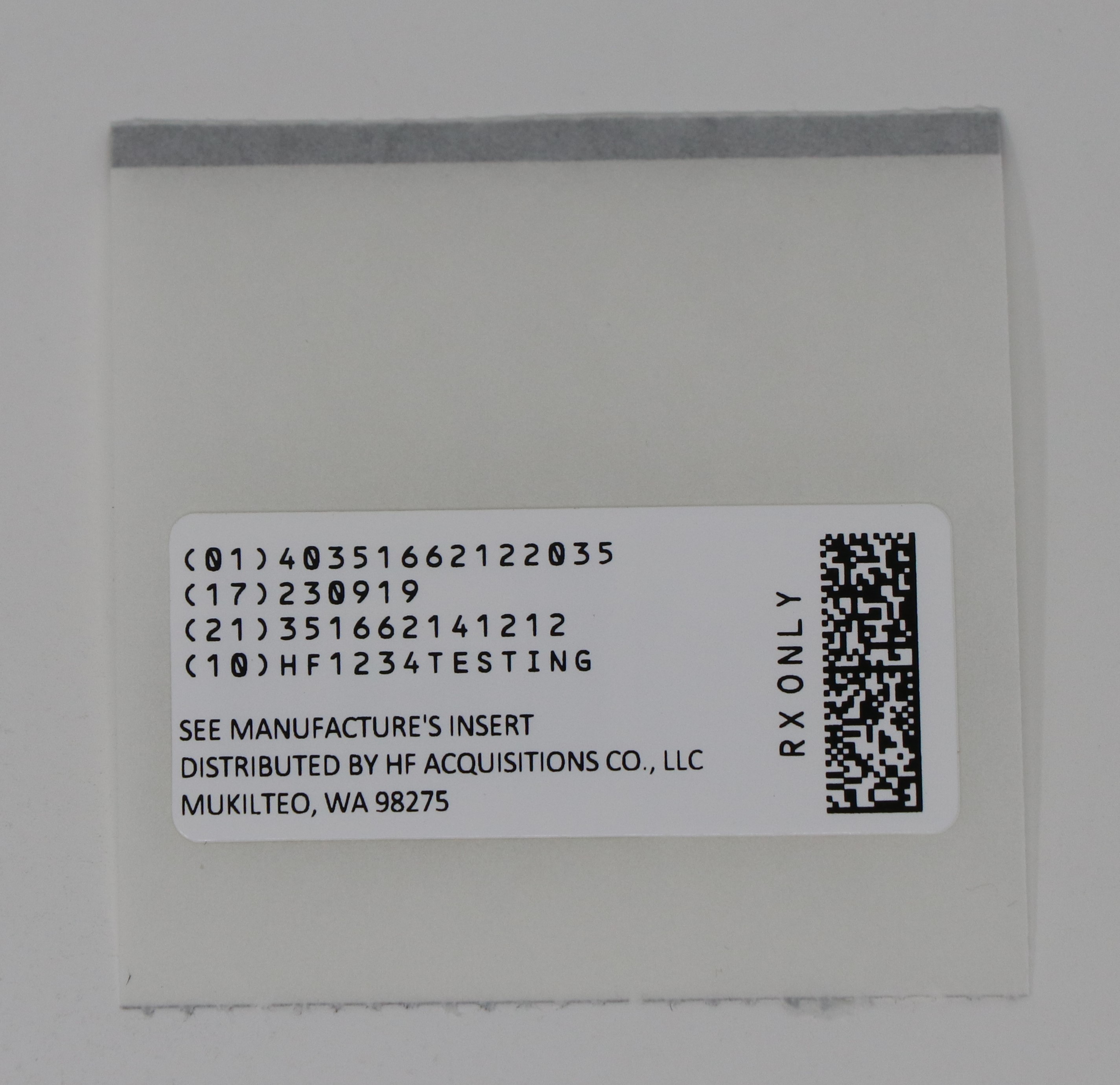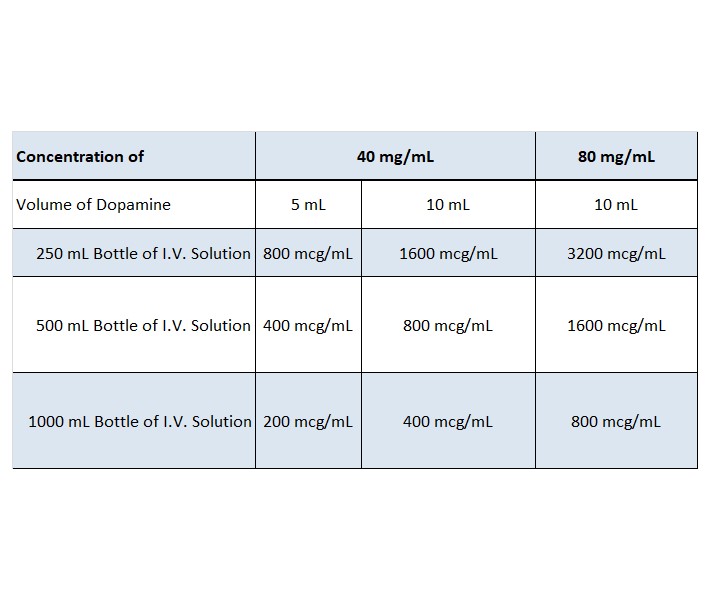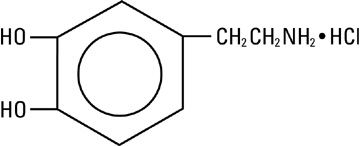 DRUG LABEL: DOPAMINE HCI
NDC: 51662-1220 | Form: INJECTION, SOLUTION, CONCENTRATE
Manufacturer: HF Acquisition Co. LLC, DBA Health First
Category: prescription | Type: HUMAN PRESCRIPTION DRUG LABEL
Date: 20240222

ACTIVE INGREDIENTS: DOPAMINE HYDROCHLORIDE 40 mg/1 mL
INACTIVE INGREDIENTS: SODIUM METABISULFITE 9 mg/1 mL; ANHYDROUS CITRIC ACID 10 mg/1 mL; TRISODIUM CITRATE DIHYDRATE 5 mg/1 mL

DOPAMINE HCI INJ., USP 400mg (40mg/mL) 10mL VIAL

SPL Unclassified

Injection, USP

Fliptop Vial
Pintop Vial

MUST BE DILUTED PRIOR TO ADMINISTRATION

Description

Dopamine, a sympathomimetic amine vasopressor, is the naturally occurring immediate precursor of norepinephrine. Dopamine hydrochloride is a white to off-white crystalline powder, which may have a slight odor of hydrochloric acid. It is freely soluble in water and soluble in alcohol. Dopamine HCl is sensitive to alkalies, iron salts, and oxidizing agents. Chemically it is designated as 4-(2-aminoethyl) pyrocatechol hydrochloride, and its molecular formula is C8H11NO2 • HCl.

The structural formula is:

and the molecular weight is 189.64.

Dopamine hydrochloride injection is a clear, practically colorless, sterile, pyrogen-free, aqueous solution of dopamine HCl for intravenous infusion after dilution. Each milliliter of the 40 mg/mL preparation contains 40 mg of dopamine hydrochloride (equivalent to 32.31 mg of dopamine base). Each milliliter of the 80 mg/mL preparation contains 80 mg of dopamine hydrochloride (equivalent to 64.62 mg of dopamine base). Each milliliter of both preparations contains the following: Sodium metabisulfite 9 mg added as an antioxidant; citric acid, anhydrous 10 mg; and sodium citrate, dihydrate 5 mg added as a buffer. May contain additional citric acid and/or sodium citrate for pH adjustment. pH is 3.3 (2.5 to 5.0).

Dopamine must be diluted in an appropriate sterile parenteral solution before intravenous administration. (See Dosage and Administration)

Clinical Pharmacology

Dopamine is a natural catecholamine formed by the decarboxylation of 3,4-dihydroxyphenylalanine (DOPA). It is a precursor to norepinephrine in noradrenergic nerves and is also a neurotransmitter in certain areas of the central nervous system, especially in the nigrostriatal tract, and in a few peripheral sympathetic nerves.

Dopamine produces positive chronotropic and inotropic effects on the myocardium, resulting in increased heart rate and cardiac contractility. This is accomplished directly by exerting an agonist action on beta-adrenoceptors and indirectly by causing release of norepinephrine from storage sites in sympathetic nerve endings.

Dopamine's onset of action occurs within five minutes of intravenous administration, and with dopamine's plasma half-life of about two minutes, the duration of action is less than ten minutes. However, if monoamine oxidase (MAO) inhibitors are present, the duration may increase to one hour. The drug is widely distributed in the body but does not cross the blood-brain barrier to a significant extent. Dopamine is metabolized in the liver, kidney, and plasma by MAO and catechol-O-methyltransferase to the inactive compounds homovanillic acid (HVA) and 3,4-dihydroxyphenylacetic acid. About 25% of the dose is taken up into specialized neurosecretory vesicles (the adrenergic nerve terminals), where it is hydroxylated to form norepinephrine. It has been reported that about 80% of the drug is excreted in the urine within 24 hours, primarily as HVA and its sulfate and glucuronide conjugates and as 3,4-dihydroxyphenylacetic acid. A very small portion is excreted unchanged.

The predominant effects of dopamine are dose-related, although it should be noted that actual response of an individual patient will largely depend on the clinical status of the patient at the time the drug is administered. At low rates of infusion (0.5 – 2 mcg/kg/min) dopamine causes vasodilation that is presumed to be due to a specific agonist action on dopamine receptors (distinct from alpha- and beta-adrenoceptors) in the renal, mesenteric, coronary, and intracerebral vascular beds. At these dopamine receptors, haloperidol is an antagonist. The vasodilation in these vascular beds is accompanied by increased glomerular filtration rate, renal blood flow, sodium excretion, and urine flow. Hypotension sometimes occurs. An increase in urinary output produced by dopamine is usually not associated with a decrease in osmolality of the urine.

At intermediate rates of infusion (2 – 10 mcg/kg/min) dopamine acts to stimulate the beta1-adrenoceptors, resulting in improved myocardial contractility, increased SA rate and enhanced impulse conduction in the heart. There is little, if any, stimulation of the beta2-adrenoceptors (peripheral vasodilation). Dopamine causes less increase in myocardial oxygen consumption than isoproterenol, and its use is not usually associated with a tachyarrhythmia. Clinical studies indicate that it usually increases systolic and pulse pressure with either no effect or a slight increase in diastolic pressure. Blood flow to the peripheral vascular beds may decrease while mesenteric flow increases due to increased cardiac output. Total peripheral resistance (alpha effects) at low and intermediate doses is usually unchanged.

At higher rates of infusion (10 – 20 mcg/kg/min) there is some effect on alpha-adrenoceptors, with consequent vasoconstrictor effects and a rise in blood pressure. The vasoconstrictor effects are first seen in the skeletal muscle vascular beds, but with increasing doses, they are also evident in the renal and mesenteric vessels. At very high rates of infusion (above 20 mcg/kg/min), stimulation of alpha-adrenoceptors predominates and vasoconstriction may compromise the circulation of the limbs and override the dopaminergic effects of dopamine, reversing renal dilation and naturesis.

Indications and Usage

Dopamine HCl is indicated for the correction of hemodynamic imbalances present in the shock syndrome due to myocardial infarction, trauma, endotoxic septicemia, open-heart surgery, renal failure, and chronic cardiac decompensation as in congestive failure.

Patients most likely to respond adequately to dopamine HCl are those in whom physiological parameters, such as urine flow, myocardial function, and blood pressure, have not undergone profound deterioration. Multiclinic trials indicate that the shorter the time interval between onset of signs and symptoms and initiation of therapy with blood volume correction and dopamine HCl, the better the prognosis. Where appropriate, blood volume restoration with a suitable plasma expander or whole blood should be accomplished prior to administration of dopamine HCl.

Poor Perfusion of Vital Organs – Urine flow appears to be one of the better diagnostic signs by which adequacy of vital organ perfusion can be monitored. Nevertheless, the physician should also observe the patient for signs of reversal of confusion or reversal of comatose condition. Loss of pallor, increase in toe temperature, and/or adequacy of nail bed capillary filling may also be used as indices of adequate dosage. Clinical studies have shown that when dopamine HCl is administered before urine flow has diminished to levels of approximately 0.3 mL/minute, prognosis is more favorable. Nevertheless, in a number of oliguric or anuric patients, administration of dopamine HCl has resulted in an increase in urine flow, which in some cases reached normal levels. Dopamine HCl may also increase urine flow in patients whose output is within normal limits and thus may be of value in reducing the degree of pre-existing fluid accumulation. It should be noted that at doses above those optimal for the individual patient, urine flow may decrease, necessitating reduction of dosage.

Low Cardiac Output – Increased cardiac output is related to dopamine's direct inotropic effect on the myocardium. Increased cardiac output at low or moderate doses appears to be related to a favorable prognosis. Increase in cardiac output has been associated with either static or decreased systemic vascular resistance (SVR). Static or decreased SVR associated with low or moderate movements in cardiac output is believed to be a reflection of differential effects on specific vascular beds with increased resistance in peripheral beds (e.g., femoral) and concomitant decreases in mesenteric and renal vascular beds.

Redistribution of blood flow parallels these changes so that an increase in cardiac output is accompanied by an increase in mesenteric and renal blood flow. In many instances the renal fraction of the total cardiac output has been found to increase. Increase in cardiac output produced by dopamine is not associated with substantial decreases in systemic vascular resistance as may occur with isoproterenol.

Hypotension – Hypotension due to inadequate cardiac output can be managed by administration of low to moderate doses of dopamine HCl which have little effect on SVR. At high therapeutic doses, dopamine's alpha-adrenergic activity becomes more prominent and thus may correct hypotension due to diminished SVR. As in the case of other circulatory decompensation states, prognosis is better in patients whose blood pressure and urine flow have not undergone profound deterioration. Therefore, it is suggested that the physician administer dopamine HCl as soon as a definite trend toward decreased systolic and diastolic pressure becomes evident.

Contraindications

Dopamine HCl should not be used in patients with pheochromocytoma.

Dopamine HCl should not be administered to patients with uncorrected tachyarrhythmias or ventricular fibrillation.

Warnings

Contains sodium metabisulfite, a sulfite that may cause allergic-type reactions including anaphylactic symptoms and life-threatening or less severe asthmatic episodes in certain susceptible people. The overall prevalence of sulfite sensitivity in the general population is unknown and probably low. Sulfite sensitivity is seen more frequently in asthmatic than in nonasthmatic people.

Do NOT add dopamine HCl to any alkaline diluent solution since the drug is inactivated in alkaline solution.

Patients who have been receiving MAO inhibitors prior to the administration of dopamine HCl will require substantially reduced dosage. See Drug Interactions below.

Precautions

General

1. Monitoring – Careful monitoring of the following indices is necessary during dopamine HCl infusion, as with any adrenergic agent: blood pressure, urine flow, and, when possible, cardiac output and pulmonary wedge pressure.
2. Hypovolemia – Prior to treatment with dopamine HCl, hypovolemia should be fully corrected, if possible, with either whole blood or plasma as indicated. Monitoring of central venous pressure or left ventricular filling pressure may be helpful in detecting and treating hypovolemia.
3. Hypoxia, Hypercapnia, Acidosis – These conditions, which may also reduce the effectiveness and/or increase the incidence of adverse effects of dopamine, must be identified and corrected prior to, or concurrently with, administration of dopamine HCl.
4. Decreased Pulse Pressure – If a disproportionate increase in diastolic blood pressure and a marked decrease in pulse pressure are observed in patients receiving dopamine HCl, the rate of infusion should be decreased and the patient observed carefully for further evidence of predominant vasoconstrictor activity, unless such effect is desired.
5. Ventricular Arrhythmias – If an increased number of ectopic beats are observed, the dose should be reduced if possible.
6. Hypotension – At lower infusion rates, if hypotension occurs, the infusion rate should be rapidly increased until adequate blood pressure is obtained. If hypotension persists, dopamine HCl should be discontinued and a more potent vasoconstrictor agent such as norepinephrine should be administered.
7. Extravasation – Dopamine HCl should be infused into a large vein whenever possible to prevent the possibility of extravasation into tissue adjacent to the infusion site. Extravasation may cause necrosis and sloughing of surrounding tissue. Large veins of the antecubital fossa are preferred to veins in the dorsum of the hand or ankle. Less suitable infusion sites should be used only if the patient's condition requires immediate attention. The physician should switch to more suitable sites as rapidly as possible. The infusion site should be continuously monitored for free flow.
8. Occlusive Vascular Disease – Patients with a history of occlusive vascular disease (for example, atherosclerosis, arterial embolism, Raynaud's disease, cold injury, diabetic endarteritis, and Buerger's disease) should be closely monitored for any changes in color or temperature of the skin in the extremities. If a change in skin color or temperature occurs and is thought to be the result of compromised circulation in the extremities, the benefits of continued dopamine HCl infusion should be weighed against the risk of possible necrosis. This condition may be reversed by either decreasing the rate or discontinuing the infusion.

IMPORTANT
Antidote for Peripheral Ischemia: To prevent sloughing and necrosis in ischemic areas, the area should be infiltrated as soon as possible with 10 to 15 mL of saline solution containing from 5 to 10 mg of phentolamine mesylate, an adrenergic blocking agent. A syringe with a fine hypodermic needle should be used, and the solution liberally infiltrated throughout the ischemic area. Sympathetic blockade with phentolamine causes immediate and conspicuous local hyperemic changes if the area is infiltrated within 12 hours. Therefore, phentolamine should be given as soon as possible after the extravasation is noted.

9. Weaning – When discontinuing the infusion, it may be necessary to gradually decrease the dose of dopamine HCl while expanding blood volume with intravenous fluids, since sudden cessation may result in marked hypotension.

Drug Interactions

1. Because dopamine is metabolized by monoamine oxidase (MAO), inhibition of this enzyme prolongs and potentiates the effect of dopamine. Patients who have been treated with MAO inhibitors within two to three weeks prior to the administration of dopamine HCl should receive initial doses of dopamine HCl no greater than one-tenth (1/10) of the usual dose.
2. Concurrent administration of dopamine HCl and diuretic agents may produce an additive or potentiating effect on urine flow.
3. Tricyclic antidepressants may potentiate the pressor response to adrenergic agents.
4. Cardiac effects of dopamine are antagonized by beta-adrenergic blocking agents, such as propranolol and metoprolol. The peripheral vasoconstriction caused by high doses of dopamine HCl is antagonized by alpha-adrenergic blocking agents. Dopamine-induced renal and mesenteric vasodilation is not antagonized by either alpha- or beta-adrenergic blocking agents.
5. Haloperidol appears to have strong central antidopaminergic properties. Haloperidol and haloperidol-like drugs suppress the dopaminergic renal and mesenteric vasodilation induced at low rates of dopamine infusion.
6. Cyclopropane or halogenated hydrocarbon anesthetics increase cardiac autonomic irritability and may sensitize the myocardium to the action of certain intravenously administered catecholamines, such as dopamine. This interaction appears to be related both to pressor activity and to beta-adrenergic stimulating properties of these catecholamines and may produce ventricular arrhythmias and hypertension. Therefore, EXTREME CAUTION should be exercised when administering dopamine HCl to patients receiving cyclopropane or halogenated hydrocarbon anesthetics. It has been reported that results of studies in animals indicate that dopamine-induced ventricular arrhythmias during anesthesia can be reversed by propranolol.
7. The concomitant use of vasopressors and some oxytocic drugs may result in severe persistent hypertension. See Labor and Delivery below.
8. Administration of phenytoin to patients receiving dopamine HCl has been reported to lead to hypotension and bradycardia. It is suggested that in patients receiving dopamine HCl, alternatives to phenytoin should be used if anticonvulsant therapy is needed.

Pregnancy: Teratogenic Effects: Animal studies have revealed no evidence of teratogenic effects due to dopamine. However, in one study, administration of dopamine HCl to pregnant rats resulted in a decreased survival rate of the newborn and a potential for cataract formation in the survivors. There are no adequate and well-controlled studies in pregnant women and it is not known if dopamine crosses the placental barrier. Because animal reproduction studies are not always predictive of human response, this drug should be used during pregnancy only if, in the judgment of the physician, the potential benefit justifies the potential risk to the fetus.

Labor and Delivery

In obstetrics, if vasopressor drugs are used to correct hypotension or are added to a local anesthetic solution, some oxytocic drugs may cause severe persistent hypertension and may even cause rupture of a cerebral blood vessel to occur during the postpartum period.

Nursing Mothers

It is not known whether this drug is excreted in human milk. Because many drugs are excreted in human milk, caution should be exercised when dopamine HCl is administered to a nursing woman.

Pediatric Use

Safety and effectiveness in children have not been established. Dopamine HCl has been used in a limited number of pediatric patients, but such use has been inadequate to fully define proper dosage and limitations for use.

Adverse Reactions

The following adverse reactions have been observed, but there are not enough data to support an estimate of their frequency.

Cardiovascular System:

ventricular arrhythmia
atrial fibrillation
ectopic beats
tachycardia
anginal pain
palpitation
cardiac conduction abnormalities
widened QRS complex
bradycardia
hypotension
hypertension
vasoconstriction

Respiratory System:

dyspnea

Gastrointestinal System:

nausea
vomiting

Metabolic/Nutritional System:

azotemia

Central Nervous System:

headache
anxiety

Dermatological System:

piloerection

Other:

Gangrene of the extremities has occurred when high doses were administered for prolonged periods or in patients with occlusive vascular disease receiving low doses of dopamine HCl.

Overdosage

In the case of accidental overdosage, as evidenced by excessive elevation of blood pressure, reduce rate of administration or temporarily discontinue dopamine HCl until patient's condition stabilizes. Since dopamine's duration of action is quite short, no additional remedial measures are usually necessary. If these measures fail to stabilize the patient's condition, use of the short-acting alpha-adrenergic blocking agent phentolamine should be considered.

Dosage and Administration

WARNING: This is a potent drug; it must be diluted before administration to the patient.

Dopamine Hydrochloride Injection, USP is administered (only after dilution) by intravenous infusion.

Suggested Dilution – For the 40 mg/mL preparation, transfer by aseptic technique the contents containing either 5 mL, 200 mg or 10 mL, 400 mg of Dopamine Hydrochloride to either a 250 mL or 500 mL bottle of one of the sterile intravenous solutions listed below. For the 80 mg/mL preparation, transfer by aseptic technique the contents containing 10 mL, 800 mg of Dopamine Hydrochloride to a 250 mL, 500 mL or 1000 mL bottle of one of the following sterile intravenous solutions:

0.9% Sodium Chloride Injection, USP
5% Dextrose Injection, USP
5% Dextrose and 0.9% Sodium Chloride Injection, USP
5% Dextrose and 0.45% Sodium Chloride Injection, USP
5% Dextrose and Lactated Ringer's Injection
Sodium Lactate Injection, USP 1/6 Molar
Lactated Ringer's Injection, USP

The resultant dilutions are summarized in the following chart:

Dopamine Hydrochloride Injection, USP has been found to be stable for a minimum of 24 hours after dilution in the foregoing intravenous solutions. However, as with all intravenous admixtures, dilution should be made just prior to administration.

Do NOT add Dopamine Hydrochloride to Sodium Bicarbonate Injection, USP or other alkaline intravenous solutions, since the drug is inactivated in alkaline solution.

Rate of Administration – Dopamine Hydrochloride Injection, USP after dilution, is administered intravenously by infusion via a suitable intravenous catheter or needle. When administering Dopamine Hydrochloride (or any potent medication) by continuous intravenous infusion, it is advisable to use a precision volume control intravenous set. Each patient must be individually titrated to the desired hemodynamic or renal response to dopamine.

In titrating to the desired increase in systolic blood pressure, the optimum dosage rate for renal response may be exceeded, thus necessitating a reduction in rate after the hemodynamic condition is stabilized.

Administration at rates greater than 50 mcg/kg/min have safely been used in advanced circulatory decompensation states. If unnecessary fluid expansion is of concern, adjustment of drug concentration may be preferred over increasing the flow rate of a less concentrated dilution.

Suggested Regimen:

1. When appropriate, increase blood volume with whole blood or plasma until central venous pressure is 10 to 15 cm H 2O or pulmonary wedge pressure is 14 to 18 mm Hg.
2. Begin infusion of diluted solution at doses of 2 – 5 mcg/kg/min of Dopamine Hydrochloride in patients who are likely to respond to modest increments of heart force and renal perfusion.
In more seriously ill patients, begin infusion of diluted solution at doses of 5 mcg/kg/min of Dopamine Hydrochloride and increase gradually using 5 to 10 mcg/kg/min increments up to a rate of 20 to 50 mcg/kg/min as needed. If doses in excess of 50 mcg/kg/min are required, it is advisable to check urine output frequently. Should urinary flow begin to decrease in the absence of hypotension, reduction of dopamine dosage should be considered. Multiclinic trials have shown that more than 50 percent of patients have been satisfactorily maintained on doses less than 20 mcg/kg/min.
In patients who do not respond to these doses with adequate arterial pressures or urine flow, additional increments of dopamine may be given in an effort to produce an appropriate arterial pressure and central perfusion.
3. Treatment of all patients requires constant evaluation of therapy in terms of blood volume, augmentation of cardiac contractility, and distribution of peripheral perfusion.
Dosage of dopamine should be adjusted according to the patient's response, with particular attention to diminution of established urine flow rate, increasing tachycardia or development of new dysrhythmias as indices for decreasing or temporarily suspending the dosage.
4. As with all potent intravenously administered drugs, care should be taken to control the rate of administration to avoid inadvertent administration of a bolus of the drug.
Parenteral drug products should be inspected visually for particulate matter and discoloration prior to administration, whenever solution and container permit.

How Supplied

DOPAMINE HCI INJ., USP is supplied in the following dosage forms.
NDC 51662-1220-1
DOPAMINE HCI INJ., USP 400mg (40mg/mL) 10mL VIAL

NDC 51662-1220-2
DOPAMINE HCI INJ., USP 400mg (40mg/mL) 10mL VIAL, 1 VIAL PER POUCH

NDC 51662-1220-3
DOPAMINE HCI INJ., USP 400mg (40mg/mL) 10mL VIAL, 1 VIAL PER POUCH, 25 POUCHES PER CASE

HF Acquisition Co LLC, DBA HealthFirst
Mukilteo, WA 98275

Avoid contact with alkalies (including sodium bicarbonate), oxidizing agents or iron salts.

Do not use the injection if it is darker than slightly yellow or discolored in any other way.

Store at 20 to 25°C (68 to 77°F). [See USP Controlled Room Temperature.]

Distributed by Hospira, Inc., Lake Forest, IL 60045 USA [Hospira Logo]

LAB-1154-1.0

Revised: 03/2018

PRINCIPAL DISPLAY PANEL 51662-1220-2 POUCH

VIAL

POUCH LABEL

PRINCIPAL DISPLAY PANEL 51662-1220-3 CASE

CASE LABELING

SERIALIZED RFID